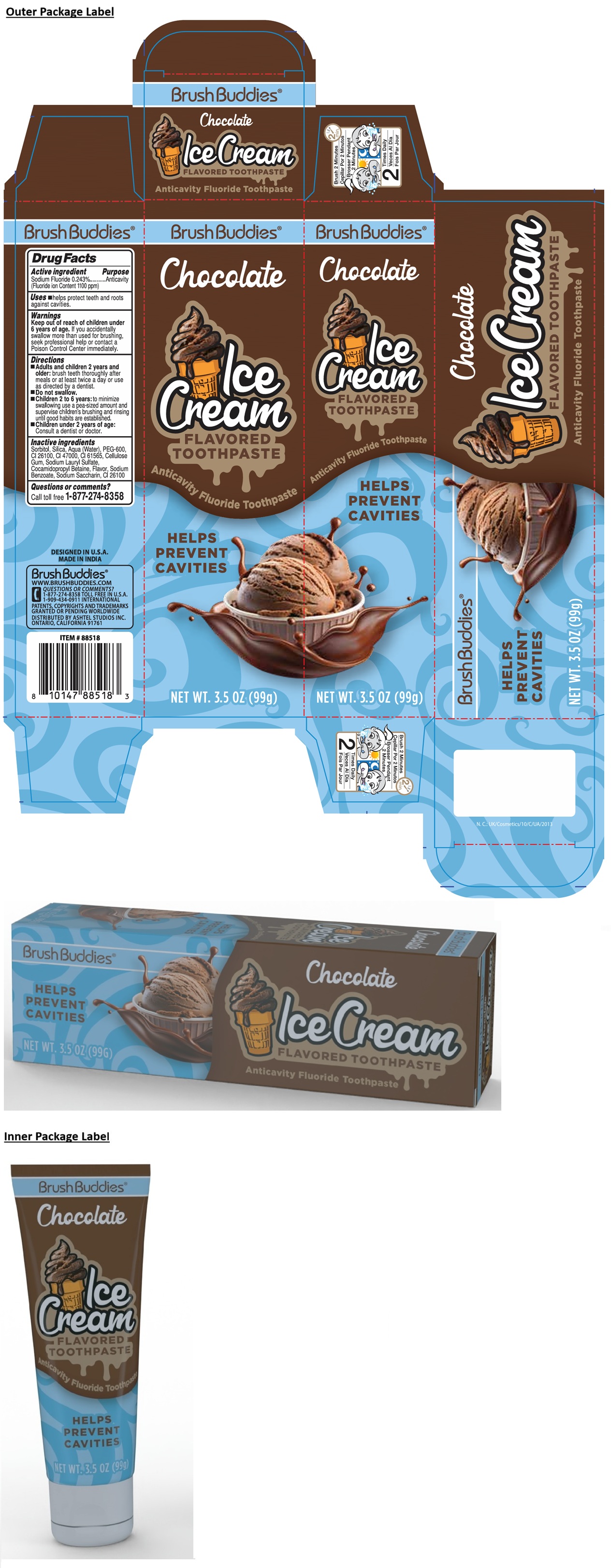 DRUG LABEL: Brush Buddies Chocolate Ice Cream FLAVORED Anticavity Fluoride
NDC: 70108-236 | Form: PASTE, DENTIFRICE
Manufacturer: Ashtel Studios, Inc.
Category: otc | Type: HUMAN OTC DRUG LABEL
Date: 20250916

ACTIVE INGREDIENTS: SODIUM FLUORIDE 0.243 g/100 g
INACTIVE INGREDIENTS: SORBITOL; SILICON DIOXIDE; WATER; POLYETHYLENE GLYCOL 600; D&C RED NO. 17; D&C YELLOW NO. 11; D&C GREEN NO. 6; CARBOXYMETHYLCELLULOSE SODIUM, UNSPECIFIED; SODIUM LAURYL SULFATE; COCAMIDOPROPYL BETAINE; SODIUM BENZOATE; SACCHARIN SODIUM

Brush Buddies® Chocolate Ice Cream FLAVORED Anticavity Fluoride Toothpaste

Active ingredient

Sodium Fluoride 0.243%
(Fluoride ion Content 1100 ppm)

Purpose

Anticavity

Uses

• helps protect teeth and roots against cavities.

Warnings

Keep out of reach of children under 6 years of age. If you accidentally swallow more than used for brushing, seek professional help or contact a Poison Control Center immediately.

Directions

• Adults and children 2 years and older: brush teeth thoroughly after meals or at least twice a day or use as directed by a dentist.
• Do not swallow.
• Children 2 to 6 years: to minimize swallowing use a pea-sized amount and supervise children's brushing and rinsing until good habits are established.
• Children under 2 years of age: Consult a dentist or doctor.

Inactive ingredients

Sorbitol, Silica, Aqua (Water), PEG-600, CI 26100, CI 47000, CI 61565, Cellulose Gum, Sodium Lauryl Sulfate, Cocamidopropyl Betaine, Flavor, Sodium Benzoate, Sodium Saccharin, CI 26100

Questions or comments?

Call toll free 1-877-274-8358

HELPS PREVENT CAVITIES

DESIGNED IN U.S.A.
MADE IN INDIA

WWW.BRUSHBUDDIES.COM
1-909-434-0911 INTERNATIONAL

PATENTS, COPYRIGHTS AND TRADEMARKS GRANTED OR PENDING WORLDWIDE
DISTRIBUTED BY ASHTEL STUDIOS INC.
ONTARIO, CALIFORNIA 91761

Brush 2 Minutes

2 Times Daily